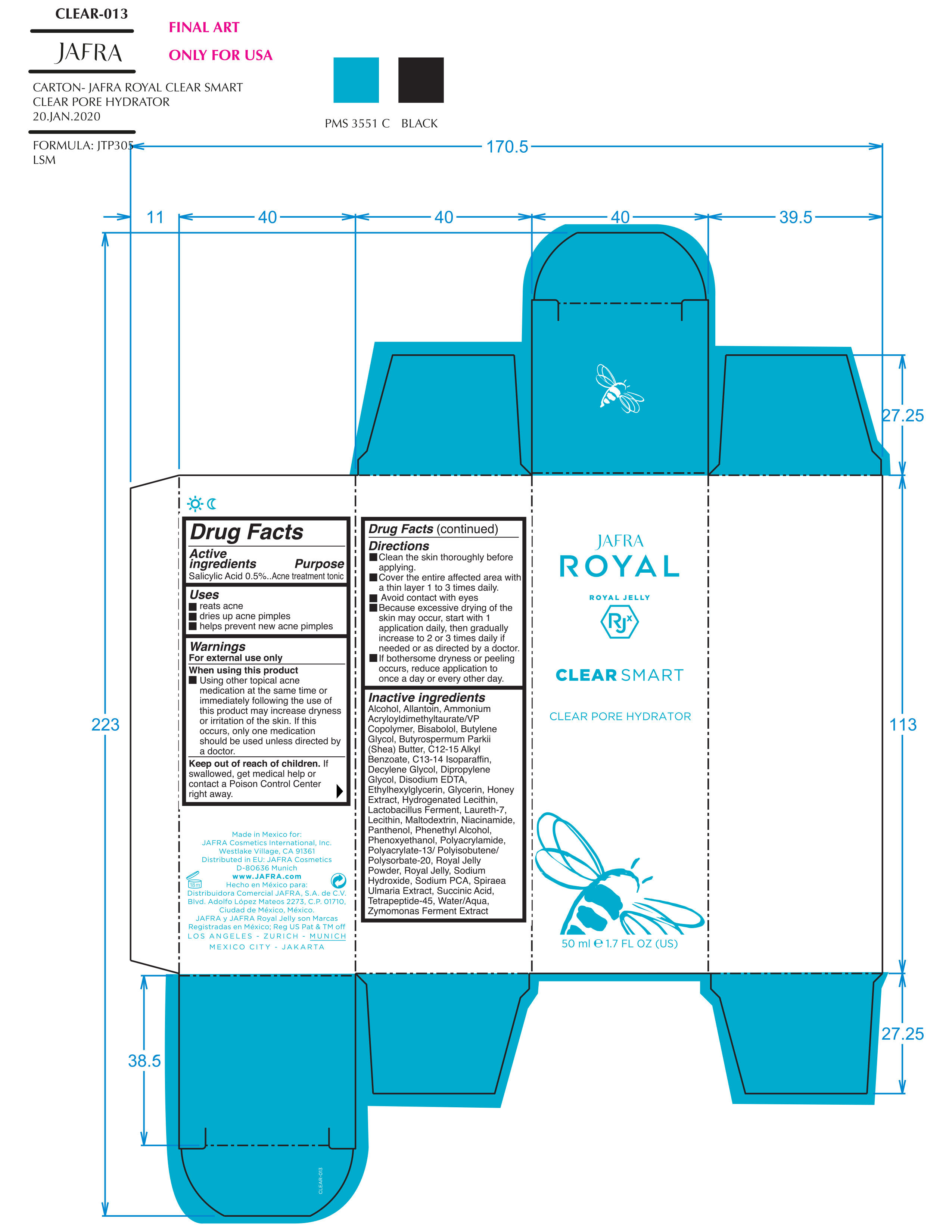 DRUG LABEL: Clear Smart Clear Pore Hydrator
NDC: 68828-249 | Form: GEL
Manufacturer: Jafra Cosmetics International Inc
Category: otc | Type: HUMAN OTC DRUG LABEL
Date: 20200512

ACTIVE INGREDIENTS: SALICYLIC ACID 0.5 g/100 mL
INACTIVE INGREDIENTS: DECYLENE GLYCOL; PHENYLETHYL ALCOHOL; MALTODEXTRIN; SODIUM HYDROXIDE; PANTHENOL; HYDROGENATED SOYBEAN LECITHIN; HONEY; LACTOBACILLUS REUTERI; POLYACRYLAMIDE (1500 MW); ROYAL JELLY; SODIUM PYRROLIDONE CARBOXYLATE; SHEA BUTTER; C13-14 ISOPARAFFIN; SUCCINIC ACID; WATER; ALKYL (C12-15) BENZOATE; AMMONIUM ACRYLOYLDIMETHYLTAURATE/VP COPOLYMER; NIACINAMIDE; ALLANTOIN; DIPROPYLENE GLYCOL; LECITHIN, SOYBEAN; EDETATE DISODIUM; LAURETH-7; PHENOXYETHANOL; ETHYLHEXYLGLYCERIN; GLYCERIN; LEVOMENOL; BUTYLENE GLYCOL

Clear Smart Clear Pore Hydrator

Active ingredient Purpose

Salicylic Acid 0.5% Acne treatment tonic

Uses

- Treats acne
- dries up acne pimples
- helps prevent new acne pimples

Keep out of reach of children. If swallowed, get medical help or contact a Poison Control Center right away.

When using this product

Using other topical acne medication at the same time or immediately following the use of this product may increase dryness of irritation of the skin. If this occurs, only one medication should be used unless directed by a doctor.

Warnings

For external use only

Directions

- Clean the skin thoroughly before applying
- Cover the entire affected area with a thin layer 1 to 3 times daily
- Avoid contact with eyes.
- Becuase excessive drying may of the skin may occur, start with 1 application daily if needed or as directed by a doctor
- If bothersome dryness or peeling occurs, reduce application to once a day or every other day.

Inactive ingredients

Alcohol, Allantoin, Ammonium Acryloyldimethyltaurate/VP Copolymer, Bisabolol, Butylene Glycol, Butyrospermum Parkii (Shea) Butter, C12-15 Alkyl Benzoate, C13-14 Isoparaffin, Decylene Glycol, Dipropylene Glycol, Disodium EDTA, Ethylhexylglycerin, Glycerin, Honey Extract, Hydrogenated Lecithin, Lactobacillus Ferment, Laureth-7, Lecithin, Maltodextrin, Niacinamide, Panthenol, Phenethyl Alcohol, Phenoxyethanol, Polyacrylamide, Polyacrylate-13/Polyisobutene/Polysorbate-20, Royal Jelly Powder, Royal Jelly, Sodium Hydroxide, Sodium PCA,Spiraea Ulmaria Extract, Succinic Acid, Tetrapeptide-45, Water/Aqua, Zymomonas Ferment Extract

PACKAGE LABEL

Jafra Royal

Clear Smart

Clear Pore Hydrator

50ml e 1.7 FL OZ (US)